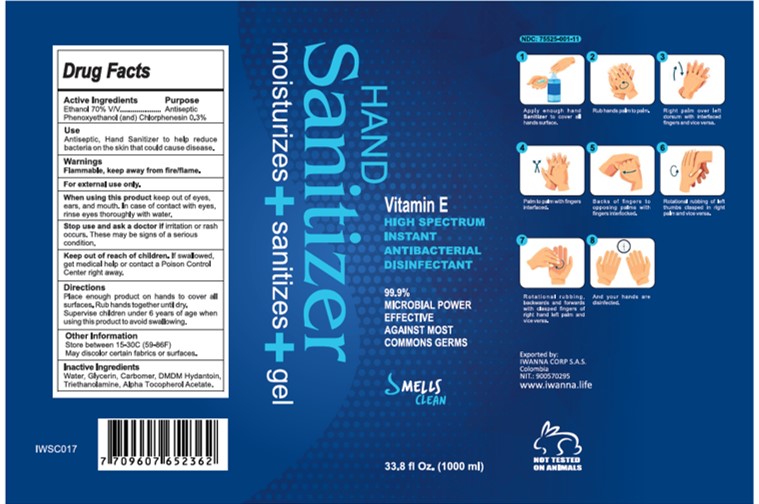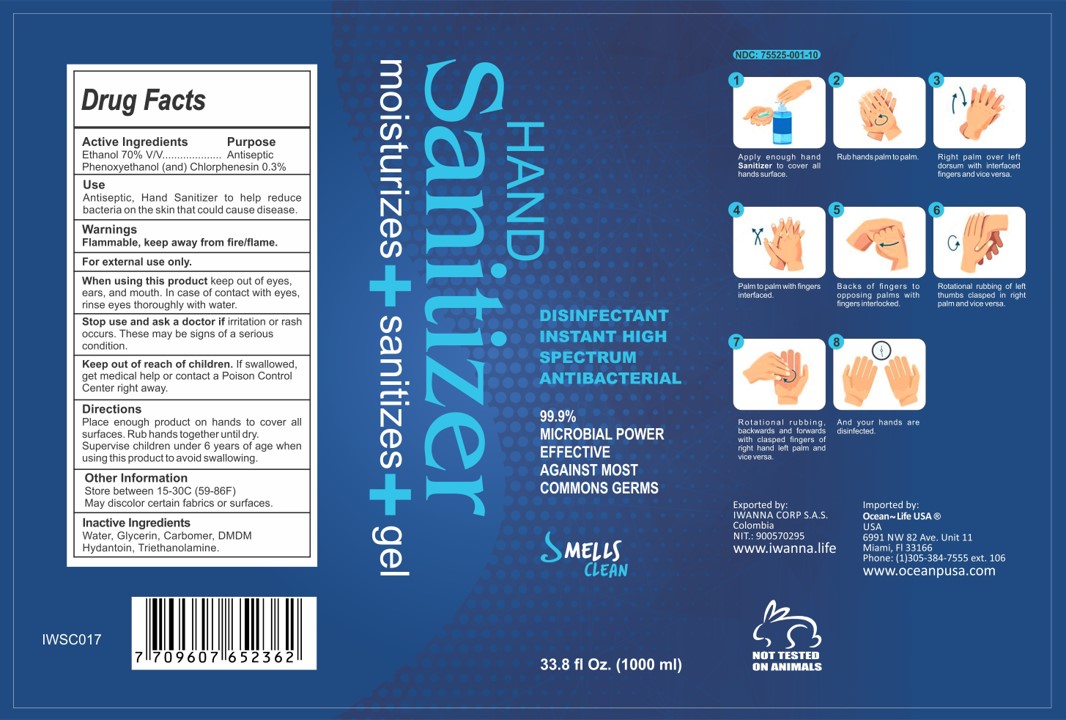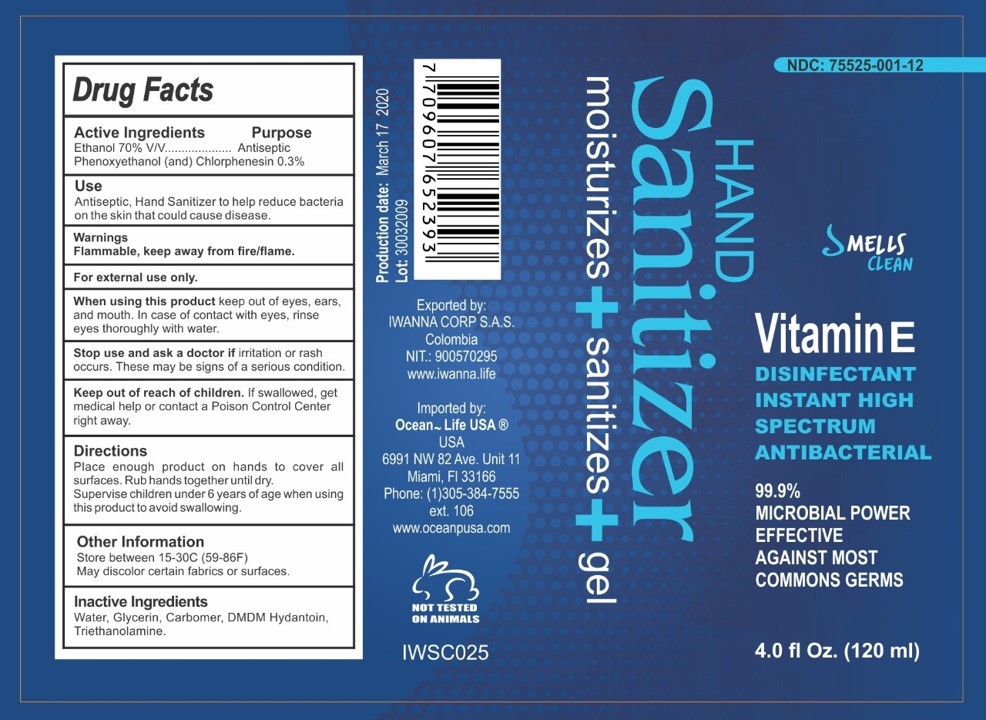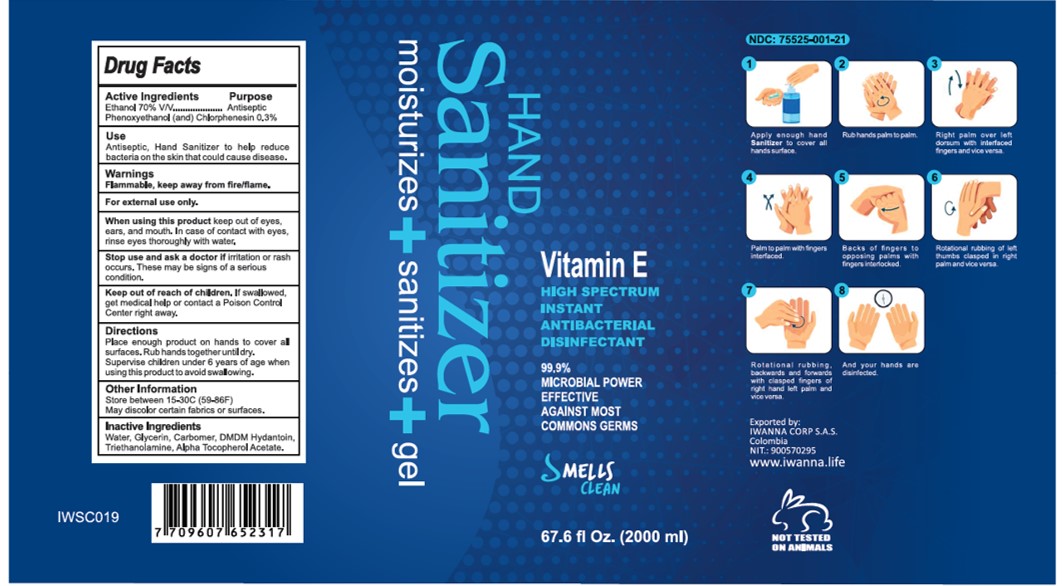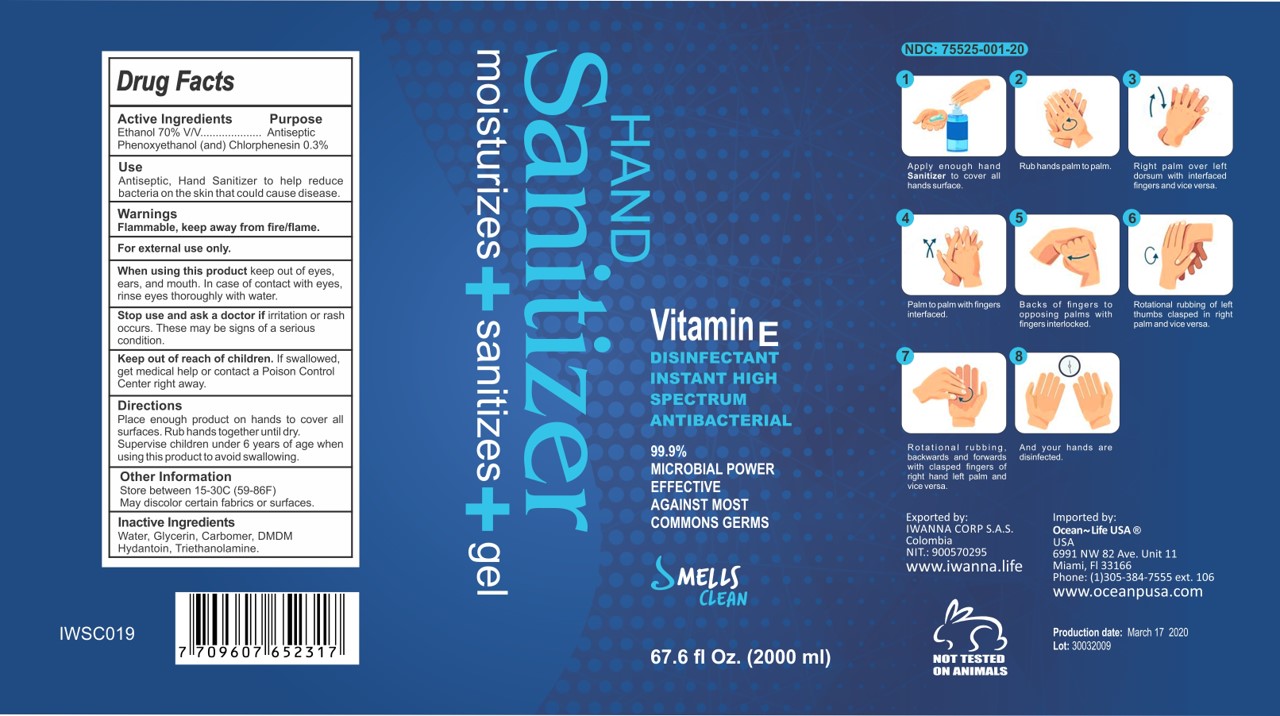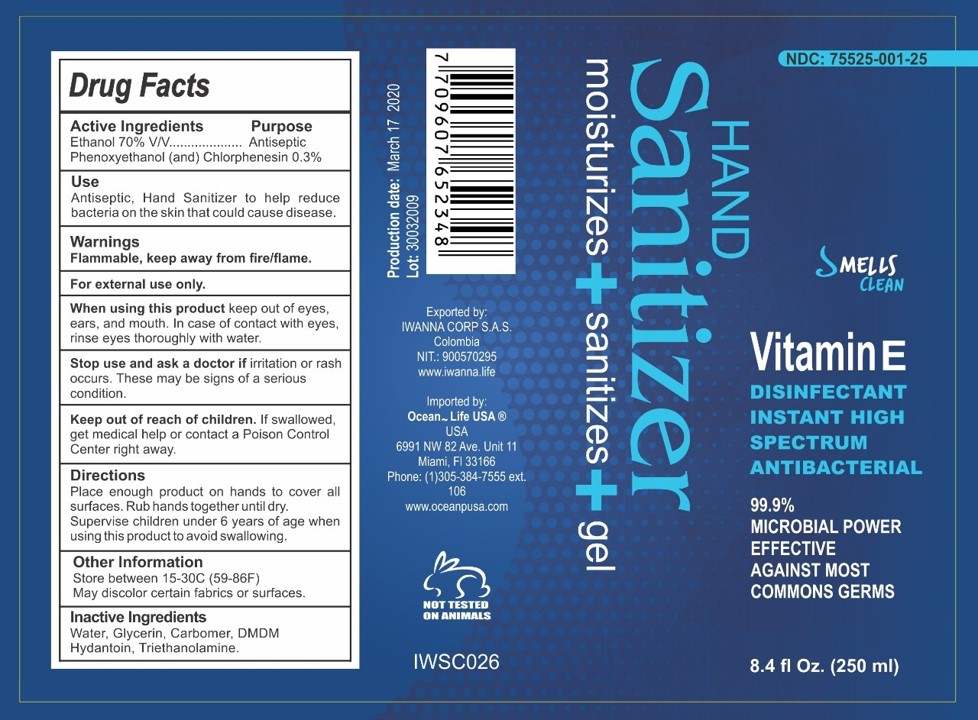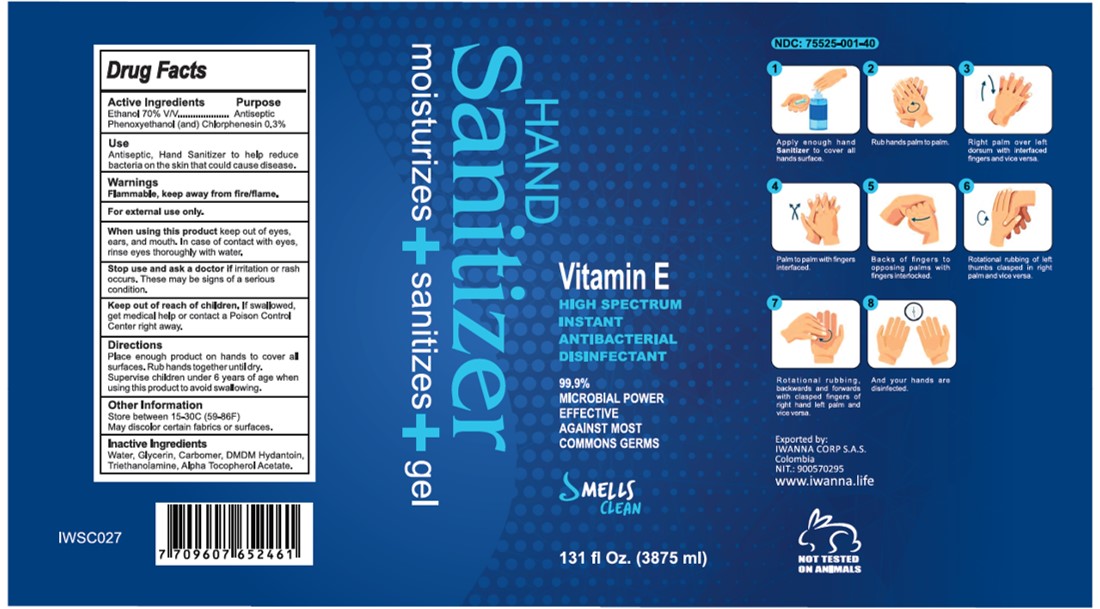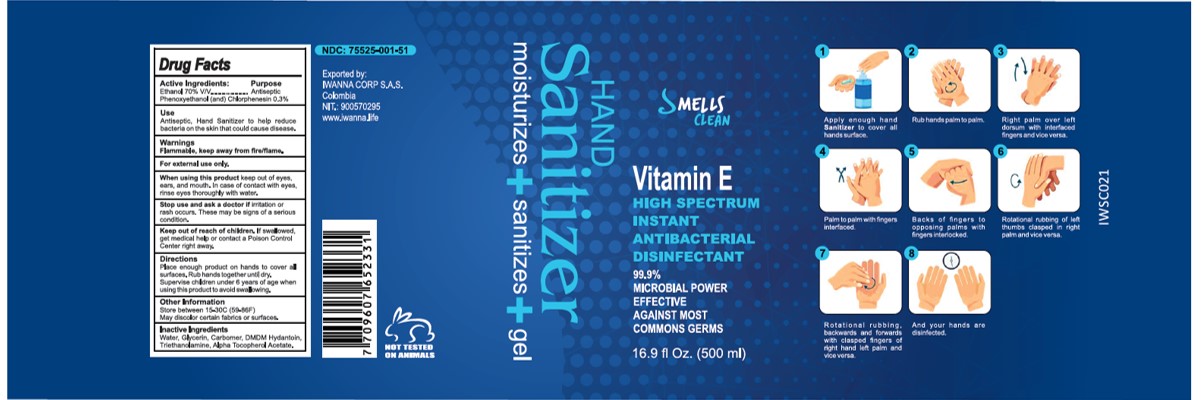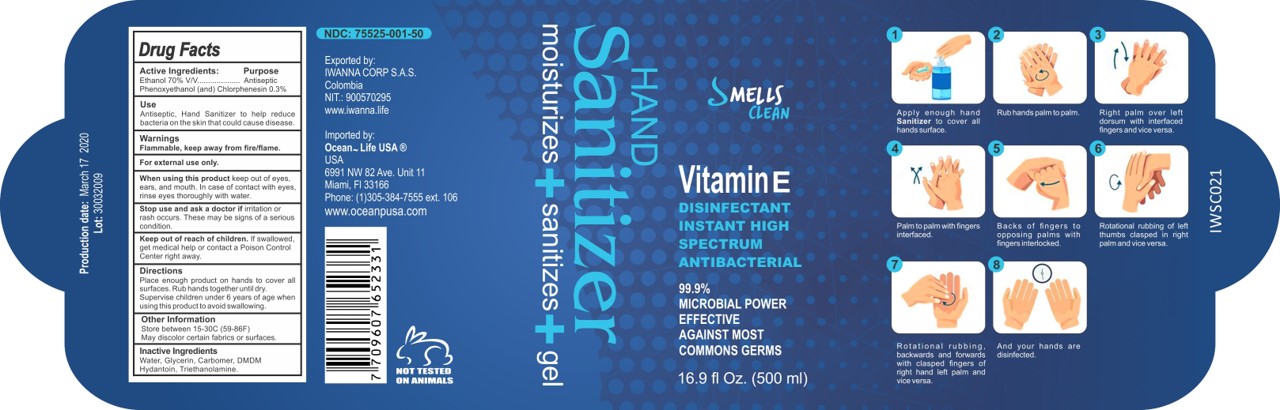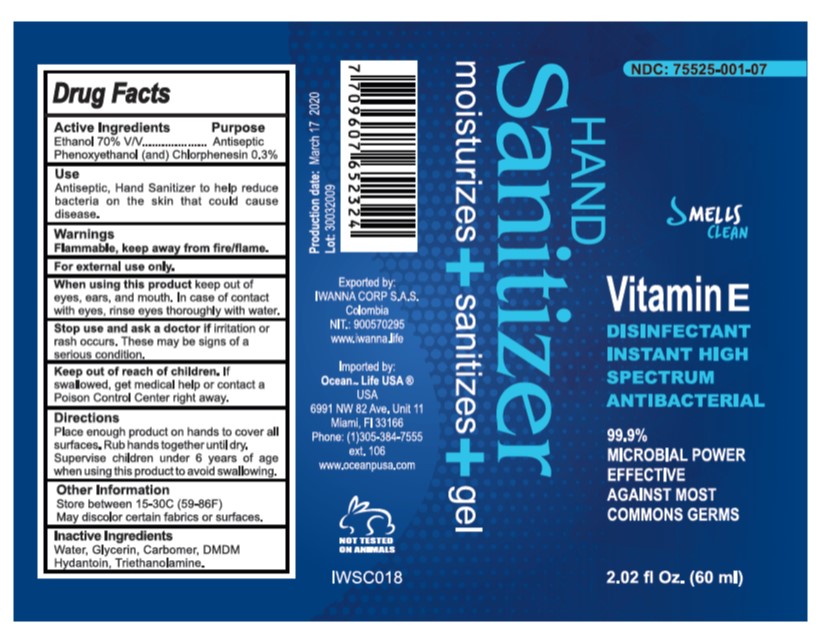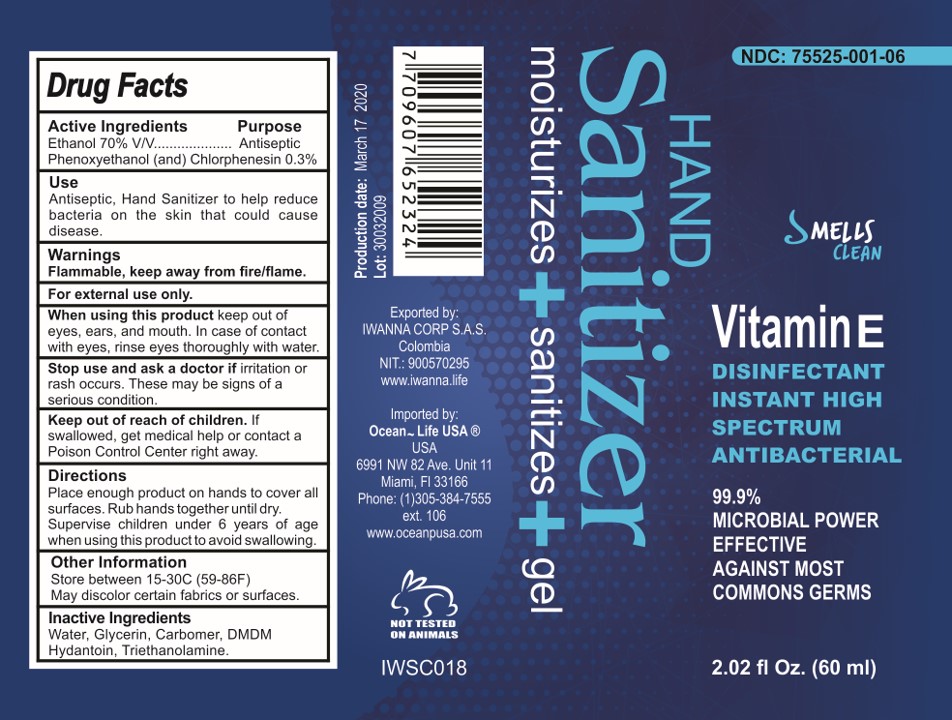 DRUG LABEL: Hand Sanitizer Smells Clean
NDC: 75525-001 | Form: GEL
Manufacturer: IWANNA CORP SAS
Category: otc | Type: HUMAN OTC DRUG LABEL
Date: 20201202

ACTIVE INGREDIENTS: CHLORPHENESIN 0.143 g/100 mL; ALCOHOL 70 mL/100 mL; PHENOXYETHANOL 0.143 g/100 mL
INACTIVE INGREDIENTS: CARBOMER 940 0.2685 g/100 mL; GLYCERIN 0.95 g/100 mL; WATER 27.8 mL/100 mL; .ALPHA.-TOCOPHEROL ACETATE 0.009 g/100 mL; TROLAMINE 0.479 g/100 mL; DMDM HYDANTOIN 0.095 g/100 mL

HAND SANITIZER

HAND SANITIZER

This is a hand sanitizer manufactured according to the Temporary Policy for Preparation of Certain Alcohol-Based Hand Sanitizer Products During the Public Health Emergency (CoViD-19); Guidance for Industry.

The hand sanitizer is manufactured using only the following United States Pharmacopoeia (USP) grade ingredients in the preparation of the product (percentage in final product formulation) consistent with World Health Organization (WHO) recommendations:

1. Alcohol (ethanol) (USP or Food Chemical Codex (FCC) grade) (70%, volume/volume (v/v)) in an aqueous solution denatured according to Alcohol and Tobacco Tax and Trade Bureau regulations in 27 CFR part 20.
2. Glycerol (1.00% v/v).
3. Phenoxyethanol and chlorphenesin (0.3% v/v).
4. Sterile distilled water or boiled cold water.

Active Ingredient(s)

Alcohol 70% v/v. Purpose: Antiseptic

Phenoxyethanol (and) chlorphenesin: 0.3%

Purpose

Antiseptic, Hand Sanitizer

To help reduce bacteria on the skin that could cause disease.

Indications and Usage

Apply enough hand Sanitizer to cover all hands surface
Rub hands palm to palm
Right palm over left dorsum with interfaced fingers and vice versa.
Palm to palm with fingers interfaced.
Backs of fingers to opposing palms with fingers interlocked.
Rotational rubbing of left thumbs clasped in right palmed and vice versa.
Rotational rubbing backwards and forwards with clasped fingers of right hand and left palm and vice versa.
And your hands are disinfected.

Warnings

Flammable. Keep away from fire or flame

For external use only.

When using this product keep out of eyes, ears, and mouth. In case of contact with eyes, rinse eyes thoroughly with water.

Stop use and ask a doctor if irritation or rash occurs. These may be signs of a serious condition

Keep out of reach of children. If swallowed, get medical help or contact a Poison Control Center right away.

When using this product keep out of eyes, ears, and mouth. In case of contact with eyes, rinse eyes thoroughly with water.
Stop use and ask a doctor if irritation or rash occurs. These may be signs of a serious condition.
Keep out of reach of children. If swallowed, get medical help or contact a Poison Control Center right away.

Stop use and ask a doctor if irritation or rash occurs. These may be signs of a serious condition.

Directions

- Place enough product on hands to cover all surfaces. Rub hands together until dry.
- Supervise children under 6 years of age when using this product to avoid swallowing.

Keep out of reach of children. If swallowed, get medical help or contact a Poison Control Center right away.

Other information

- Store between 15-30C (59-86F)
- May discolor certain fabrics or surfaces.

Inactive ingredients

Water, glycerin, Carbomer,DMDM Hydantoin, Triethanolamine

Package Label - Principal Display Panel

Hand Sanitizer

moisturizes+sanitizes+gel

Hand Sanitizer- 500 ML

Hand Sanitizer

moisturizes+sanitizes+gel

16.9 fl. oz (500 mL) NDC: 75525-001-50

HAND SANITIZER 60 ML

Hand Sanitizer

moisturizes+sanitizes+gel

2.02 fl. oz (60 mL) NDC: 75525-001-06

HAND SANITIZER 1000 ML

Hand Sanitizer

moisturizes+sanitizes+gel

33.8 fl. oz (1000 mL) NDC: 75525-001-10

HAND SANITIZER 2000 ML

Hand Sanitizer

moisturizes+sanitizes+gel

67.6 fl. oz (2000 mL) NDC: 75525-001-20

HAND SANITIZER 120 ML

Hand Sanitizer

moisturizes+sanitizes+gel

4.0 fl. oz (120 mL) NDC: 75525-001-12

HAND SANITIZER 250 ML

Hand Sanitizer

moisturizes+sanitizes+gel

8.4 fl. oz (250 mL) NDC: 75525-001-25

HAND SANITIZER 60 ML-DISPENSER

Hand Sanitizer

moisturizes+sanitizes+gel

2.02 FL OZ (60 ML)

NDC:75525-001-07

HAND SANITIZER 2000 ML DISP

Hand Sanitizer

moisturizes+sanitizes+gel

67.6 fl. oz (2000 mL) NDC: 75525-001-21

HAND SANITIZER 3875 ML DISP

Hand Sanitizer

moisturizes+sanitizes+gel

131 fl. oz (3875 mL) NDC: 75525-001-40

HAND SANITIZER 1000 ML DISP

Hand Sanitizer

moisturizes+sanitizes+gel

33.8 fl. oz (1000 mL) NDC: 75525-001-11

HAND SANITIZER 500 ML DISP

Hand Sanitizer

moisturizes+sanitizes+gel

16.9 fl. oz (500 mL) NDC: 75525-001-51